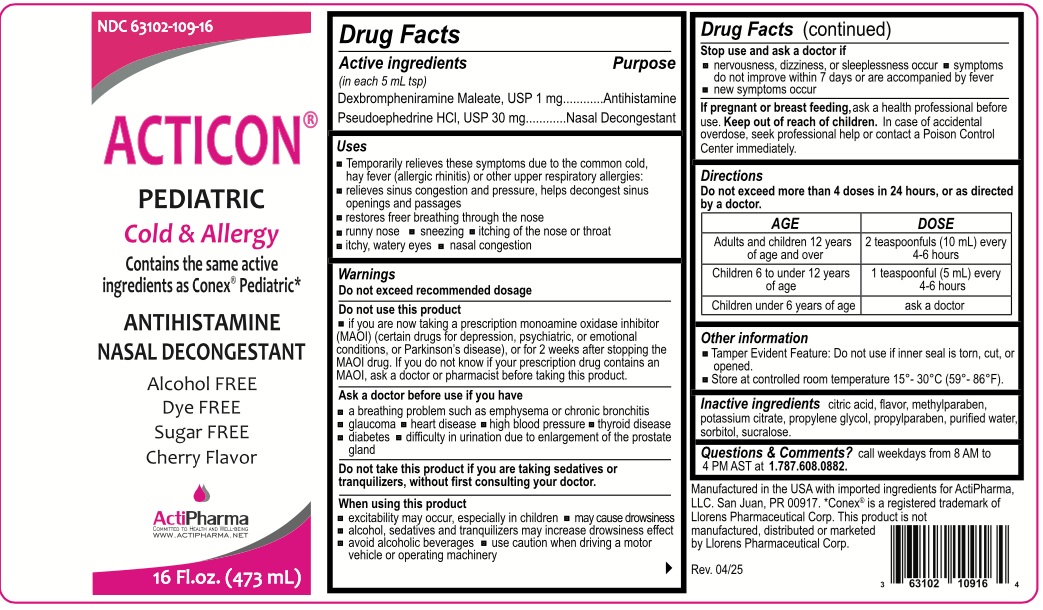 DRUG LABEL: ACTICON PEDIATRIC
NDC: 63102-109 | Form: SOLUTION
Manufacturer: ACTIPHARMA, LLC
Category: otc | Type: HUMAN OTC DRUG LABEL
Date: 20250717

ACTIVE INGREDIENTS: DEXBROMPHENIRAMINE MALEATE 1 mg/5 mL; PSEUDOEPHEDRINE HYDROCHLORIDE 30 mg/5 mL
INACTIVE INGREDIENTS: CITRIC ACID MONOHYDRATE; METHYLPARABEN; POTASSIUM CITRATE; PROPYLENE GLYCOL; PROPYLPARABEN; WATER; SORBITOL; SUCRALOSE

ACTICON® PEDIATRIC Cold & Allergy

Active ingredients (in each 5 mL tsp)

Dexbrompheniramine Maleate, USP 1 mg

Pseudoephedrine HCl, USP 30 mg

Purpose

Antihistamine

Nasal Decongestant

Uses

• Temporarily relieves these symptoms due to the common cold, hay fever (allergic rhinitis) or other respiratory allergies:
• relieves sinus congestion and pressure, helps decongest sinus openings and passages
• restores freer breathing through the nose
• runny nose • sneezing • itching of the nose or throat
• itchy, watery eyes • nasal congestion

Warnings

Do not exceed recommended dosage

Do not use this product
• if you are now taking a prescription monoamine oxidase inhibitor (MAOI) (certain drugs for depression, psychiatric, or emotional conditions, or Parkinson's disease), or for 2 weeks after stopping the MAOI drug. If you do not know if your prescription drug contains an MAOI, ask a doctor or pharmacist before taking this product.

Ask a doctor before use if you have
• a breathing problem such as emphysema or chronic bronchitis • glaucoma • heart disease • high blood pressure • thyroid disease • diabetes
• difficulty in urination due to enlargement of the prostate gland

Do not take this product if you are taking sedatives or tranquilizers, without first consulting your doctor.

When using this product
• excitability may occur, especially in children • may cause drowsiness • alcohol, sedatives and tranquilizers may increase drowsiness effect
• avoid alcoholic beverages • use caution when driving a motor vehicle or operating machinery

Stop use and ask a doctor if
• nervousness, dizziness, or sleeplessness occur • symptoms do not improve within 7 days or are accompanied by fever • new symptoms occur

If pregnant or breast feeding, ask a health professional before use.

Keep out of reach of children. In case of accidental overdose, seek professional help or contact a Poison Control Center immediately.

Directions

Do not exceed more than 4 doses in 24 hours, or as directed by a doctor.

AGE | DOSE
Adults and children 12 years of age and over | 2 teaspoonfuls (10 mL) every 4-6 hours
Children 6 to under 12 years of age | 1 teaspoonful (5 mL) every 4-6 hours
Children under 6 years of age | ask a doctor

Other information

• Tamper Evident Feature: Do not use if inner seal is torn, cut, or opened.
• Store at controlled room temperature 15°- 30°C (59°-86°F).

Inactive ingredients

citric acid, flavor, methylparaben, potassium citrate, propylene glycol, propylparaben, purified water, sorbitol, sucralose.

Questions & Comments?

call weekdays from 8 AM to 4 PM AST at 1.787.608.0882.

Contains the same active ingredients as Conex® Pediatric*

Alcohol FREE

Dye FREE

Sugar FREE

Cherry Flavor

ActiPharma
COMMITTED TO HEALTH AND WELL-BEING
WWW.ACTIPHARMA.NET

Manufactured in the USA with imported ingredients for ActiPharma, LLC. San Juan, PR 00917. *Conex® is a registered trademark of Llorens Pharmaceutical Corp. This product is not manufactured, distributed or marketed by Llorens Pharmaceutical Corp.